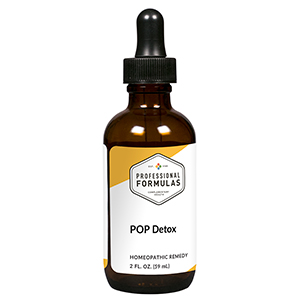 DRUG LABEL: POP Detox
NDC: 63083-6045 | Form: LIQUID
Manufacturer: Professional Complementary Health Formulas
Category: homeopathic | Type: HUMAN OTC DRUG LABEL
Date: 20190815

ACTIVE INGREDIENTS: ARCTIUM LAPPA ROOT OIL 3 [hp_X]/59 mL; MILK THISTLE 3 [hp_X]/59 mL; TRIFOLIUM PRATENSE FLOWER 3 [hp_X]/59 mL; CALENDULA OFFICINALIS FLOWERING TOP 4 [hp_X]/59 mL; EQUISETUM ARVENSE TOP 4 [hp_X]/59 mL; JUNIPERUS COMMUNIS VAR. SAXATILIS WHOLE 4 [hp_X]/59 mL; LYCOPODIUM CLAVATUM SPORE 4 [hp_X]/59 mL; RICINUS COMMUNIS SEED 4 [hp_X]/59 mL; TURPENTINE OIL 5 [hp_X]/59 mL; BERBERIS VULGARIS ROOT BARK 6 [hp_X]/59 mL; BOS TAURUS BRAIN 6 [hp_X]/59 mL; CHELIDONIUM MAJUS WHOLE 6 [hp_X]/59 mL; BOS TAURUS GALLBLADDER 6 [hp_X]/59 mL; GELSEMIUM SEMPERVIRENS ROOT 6 [hp_X]/59 mL; BEEF KIDNEY 6 [hp_X]/59 mL; BEEF LIVER 6 [hp_X]/59 mL; BOS TAURUS LYMPH VESSEL 6 [hp_X]/59 mL; PODOPHYLLUM 6 [hp_X]/59 mL; ALUMINUM 12 [hp_X]/59 mL; SILVER 12 [hp_X]/59 mL; ARSENIC TRIOXIDE 12 [hp_X]/59 mL; GOLD 12 [hp_X]/59 mL; CHOLESTEROL 12 [hp_X]/59 mL; 2,3,7,8-TETRACHLORODIBENZO-P-DIOXIN 60 [hp_X]/59 mL; METHOXYCHLOR 30 [hp_X]/59 mL; Malathion 30 [hp_X]/59 mL; HEPTACHLOR 30 [hp_X]/59 mL; HEXACHLOROBENZENE 30 [hp_X]/59 mL; FENSON 30 [hp_X]/59 mL; CAMPHECHLOR 30 [hp_X]/59 mL
INACTIVE INGREDIENTS: ALCOHOL; WATER

X45

ACTIVE INGREDIENTS

Arctium lappa 3X
Carduus marianus 3X
Trifolium pratense 3X
Calendula officinalis 4X
Equisetum arvense 4X
Juniperus communis 4X
Lycopodium clavatum 4X
Ricinus communis 4X
Terebinthina 5X
Berberis vulgaris 6X
Brain 6X
Chelidonium majus 6X
Gallbladder 6X
Gelsemium sempervirens 6X
Kidney 6X
Liver 6X
Lymph 6X
Podophyllum peltatum 6X
Aluminum metallicum 12X
Argentum metallicum 12X
Arsenicum album 12X
Aurum metallicum 12X
Cholesterinum 12X
Dioxin 60X
and all the following at 30X, 60X:
Dichlorovos methoxychlor
Endosulfan
Heptachlor
Hexachlorobenzol
Polychlorinated biphenyls
Toxaphene

QUESTIONS

Professional Formulas

PO Box 2034 Lake Oswego, OR 97035

INDICATIONS

For the temporary relief of occasional headache, nausea or vomiting, difficulty breathing, nasal irritation, skin irritation, or dizziness due to sensitivity to or exposure to persistent organic pollutants.*

PURPOSE

*Claims based on traditional homeopathic practice, not accepted medical evidence. Not FDA evaluated.

WARNINGS

Consult a doctor if condition worsens or symptoms persist. Keep out of the reach of children. In case of overdose, get medical help or contact a poison control center right away. If pregnant or breastfeeding, ask a healthcare professional before use.

Keep out of the reach of children.

PREGNANCY OR BREAST FEEDING

If pregnant or breastfeeding, ask a healthcare professional before use.

DIRECTIONS

Place drops under tongue 30 minutes before/after meals. Adults and children 12 years and over: Take 10 drops up to 3 times per day. Consult a physician for use in children under 12 years of age.

OTHER INFORMATION

Tamper resistant. If seal is broken, do not use. After opening, close container tightly and store at room temperature away from heat.

INACTIVE INGREDIENTS

20% ethanol, purified water.

LABEL

Est 1985

Professional Formulas

Complementary Health

POP Detox

Homeopathic Remedy

2 FL. OZ. (59 mL)